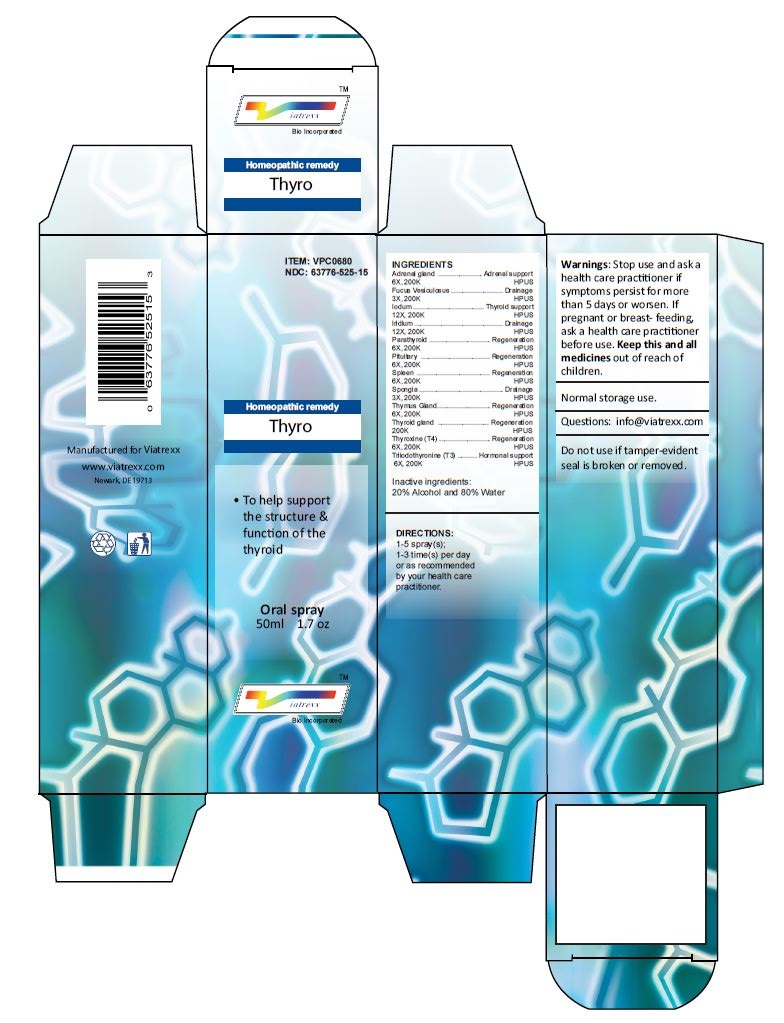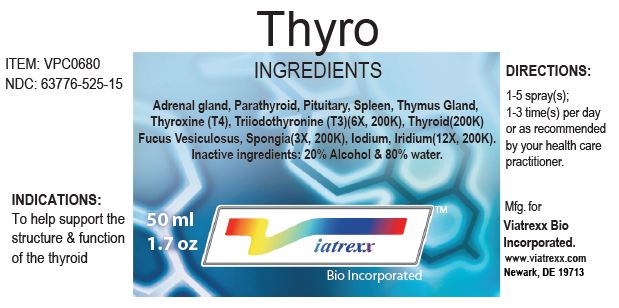 DRUG LABEL: Thyro
NDC: 63776-525 | Form: SPRAY
Manufacturer: VIATREXX BIO INCORPORATED
Category: homeopathic | Type: HUMAN OTC DRUG LABEL
Date: 20221130

ACTIVE INGREDIENTS: BOS TAURUS ADRENAL GLAND 200 [kp_C]/1 mL; SUS SCROFA ADRENAL GLAND 200 [kp_C]/1 mL; FUCUS VESICULOSUS 200 [kp_C]/1 mL; IODINE 200 [kp_C]/1 mL; IRIDIUM 200 [kp_C]/1 mL; BOS TAURUS PARATHYROID GLAND 200 [kp_C]/1 mL; SUS SCROFA PARATHYROID GLAND 200 [kp_C]/1 mL; BOS TAURUS PITUITARY GLAND 200 [kp_C]/1 mL; SUS SCROFA PITUITARY GLAND 200 [kp_C]/1 mL; BOS TAURUS SPLEEN 200 [kp_C]/1 mL; SUS SCROFA SPLEEN 200 [kp_C]/1 mL; SPONGIA OFFICINALIS WHOLE 200 [kp_C]/1 mL; BOS TAURUS THYMUS 200 [kp_C]/1 mL; SUS SCROFA THYMUS 200 [kp_C]/1 mL; THYROID, BOVINE 200 [kp_C]/1 mL; THYROID, PORCINE 200 [kp_C]/1 mL; LEVOTHYROXINE 200 [kp_C]/1 mL; LIOTHYRONINE 200 [kp_C]/1 mL
INACTIVE INGREDIENTS: ALCOHOL; WATER

Thyro

Active Ingredients

Adrenal gland 6X 200K, Fucus Vesiculosus 3X 200K, Iodum 12X 200K, Iridium 12X 200K, Parathyroid 6X 200K, Pituitary 6X 200K, Spleen 6X 200K, Spongia 3X 200K, Thymus Gland 6X 200K, Thyroid gland 200K, Thyroxine (T4) 6X 200K, Triiodothyronine (T3) 6X 200K

Purpose

Adrenal gland | Adrenal support
Fucus Vesiculosus | Drainage
Iodium | Thyroid support
Irish Moss | Regeneration
Iridium | Drainage
Parathyroid | Regeneration
Pituitary | Regeneration
Spleen | Regeneration
Spongia | Drainage
Thymus Gland | Regeneration
Thyroid gland | Regeneration
Thyroxine (T4) | Regeneration
Triiodothyronine (T3) | Hormonal support

Uses

To help support the structure & function of the thyroid

Warnings

Stop use and ask a health care practitioner if symptoms persist for more than five days or worsen. If pregnant or breastfeeding, ask a health care practitioner before use.

Dosage

1-5 spray(s); 1-3 time(s) per day or as recommended by your healthcare practitioner.

KEEP OUT OF REACH OF CHILDREN

Keep this and all medicines out of reach of children.

Other Ingredients

Alcohol and Water

Other Information

Normal storage use.
Do not use if tamper-evident seal is broken or removed.

Questions

info@viatrexx.com

Principal Display Panel

ITEM: VPC0680
NDC 63776-525-15
Homeopathic remedy
Thyro
• To help support the structure & function of the thyroid
Oral spray
50ml 1.7 oz
Viatrexx™ Bio Incorporated
Manufactured by Viatrexx
www.viatrexx.com
Newark, DE 19713

Thyro
50 mL
1.7 oz
Viatrexx™ Bio Incorporated
ITEM: VPC0680
NDC: 63776-525-15
INDICATIONS:
To help support the structure & function of the thyroid
DIRECTIONS:
1-5 spray(s); 1-3 time(s) per day or as recommended by your health care practitioner.
Mfg. for
Viatrexx Bio Incorporated.
www.viatrexx.com
Newark, DE 19713